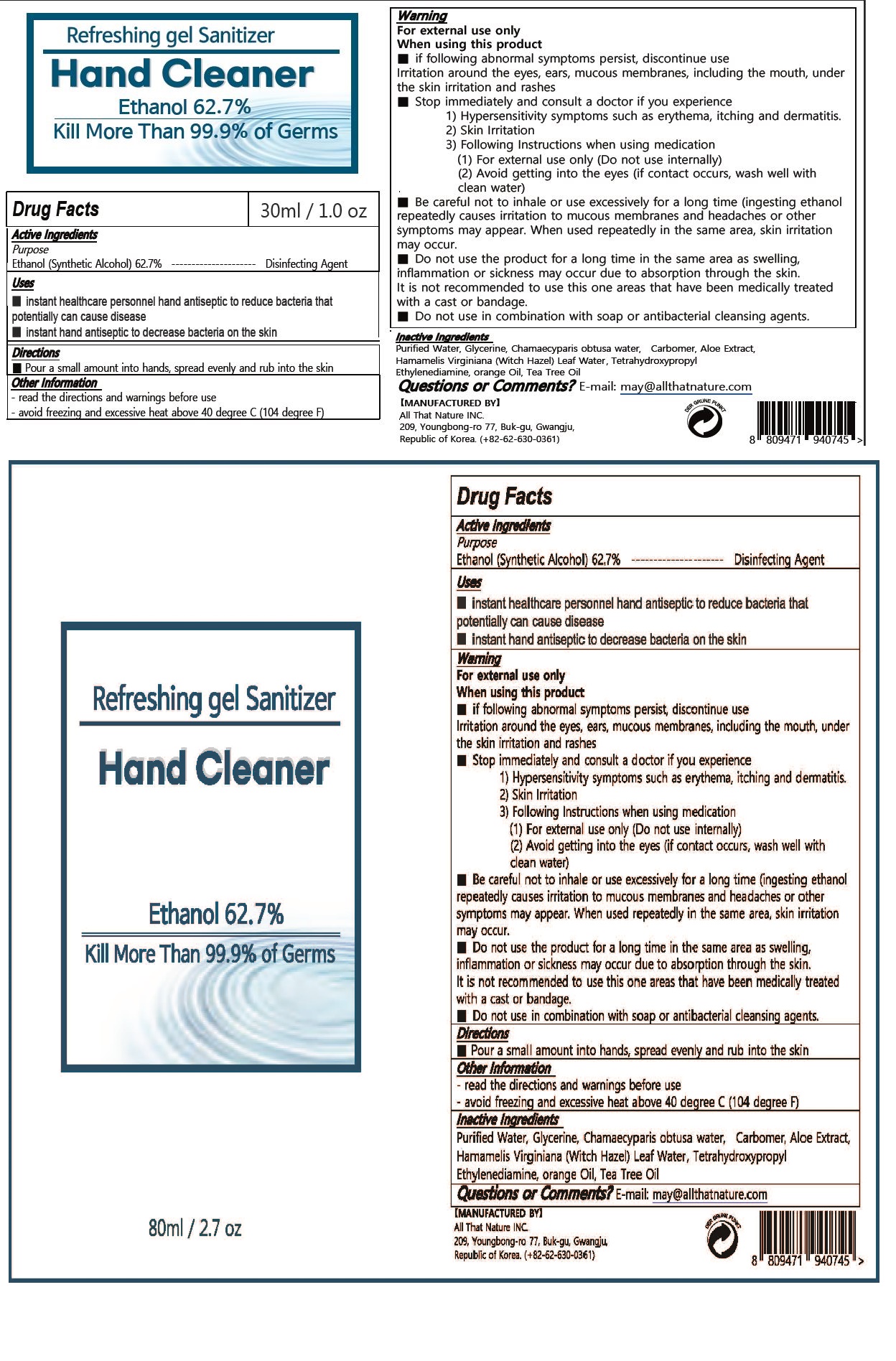 DRUG LABEL: Hand Cleaer
NDC: 79140-0001 | Form: GEL
Manufacturer: ALL THAT NATURE Co.,Ltd
Category: otc | Type: HUMAN OTC DRUG LABEL
Date: 20200717

ACTIVE INGREDIENTS: ALCOHOL 62.7 mL/100 mL
INACTIVE INGREDIENTS: WITCH HAZEL; GLYCERIN; WATER; CARBOMER 940; CHAMAECYPARIS OBTUSA WOOD; ALOE VERA LEAF

ACTIVE INGREDIENT

alcohol

INACTIVE INGREDIENT

Purified Water, Glycerine, Chamaecyparis obtusa water, Carbomer, Aloe Extract, Hamamelis Virginiana (Witch Hazel) Leaf Water, Tetrahydroxypropyl Ethylenediamine, orange Oil, Tea Tree Oil

PURPOSE

■ instant healthcare personnel hand antiseptic to reduce bacteria that potentially can cause disease

■ instant hand antiseptic to decrease bacteria on the skin

Keep out of reach of children

INDICATIONS AND USAGE

wet hands thoroughly with product and allow to dry without wiping

WARNINGS

Flammable, keep away from fire and flames
Fot external use only.

DOSAGE AND ADMINISTRATION

For external use only